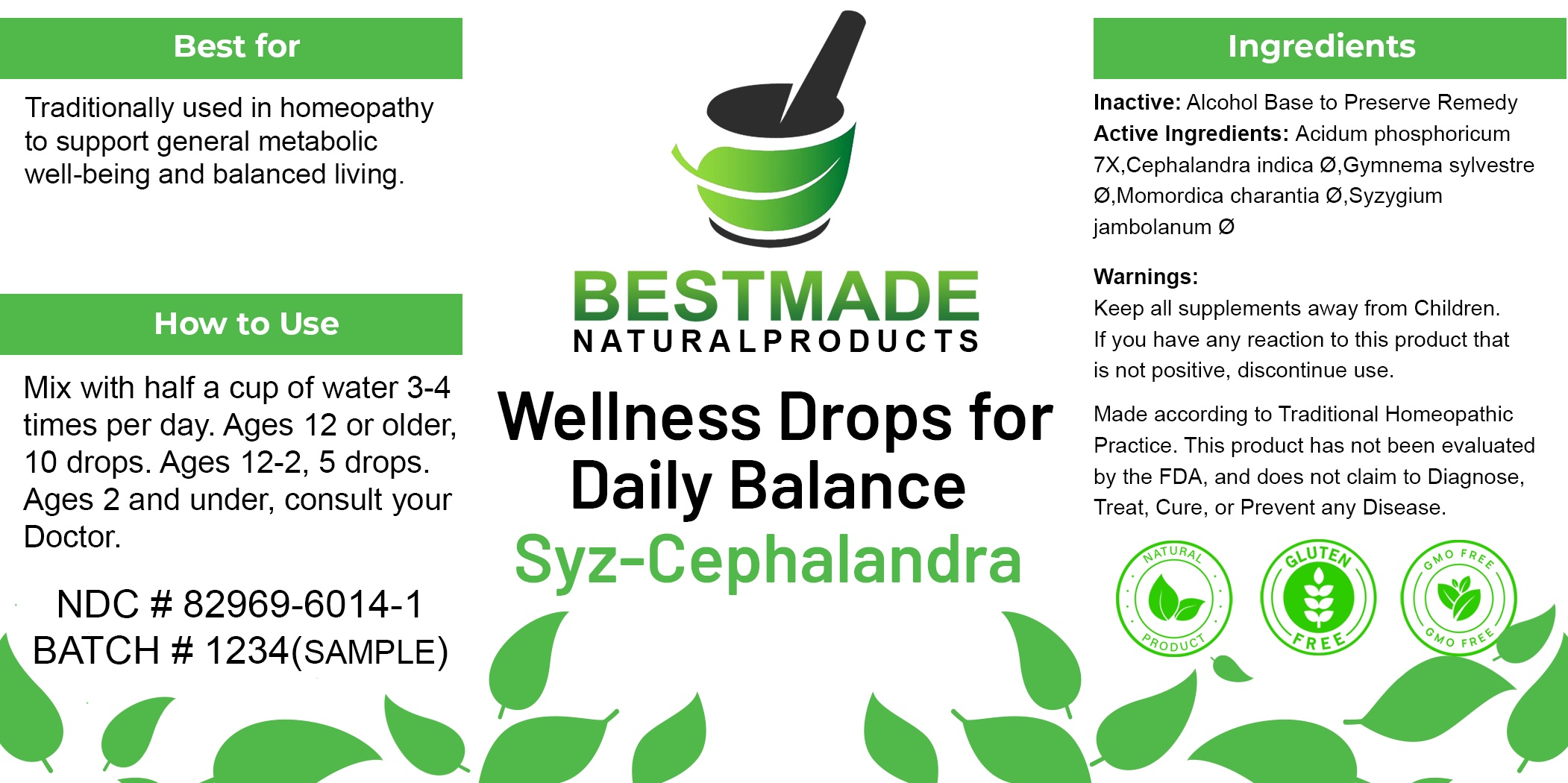 DRUG LABEL: Bestmade Natural Products - Syz-Cephalandra
NDC: 82969-6014 | Form: LIQUID
Manufacturer: Bestmade Natural Products
Category: homeopathic | Type: HUMAN OTC DRUG LABEL
Date: 20241218

ACTIVE INGREDIENTS: PHOSPHORIC ACID 30 [hp_C]/30 [hp_C]; GYMNEMA SYLVESTRE WHOLE 30 [hp_C]/30 [hp_C]; MOMORDICA CHARANTIA WHOLE 30 [hp_C]/30 [hp_C]; SYZYGIUM CUMINI SEED 30 [hp_C]/30 [hp_C]; COCCINIA GRANDIS WHOLE 30 [hp_C]/30 [hp_C]
INACTIVE INGREDIENTS: ALCOHOL 30 [hp_C]/30 [hp_C]

Daily Balance - Syz-Cephalandra

DOSAGE AND ADMINISTRATION

Mix with half a cup of water 3-4 times per day. Ages 12 or older, 10-15 drops. Ages 12-2, 5 drops. Ages 2 and under, consult your Doctor.

INDICATIONS AND USAGE

Traditionally used in homeopathy to support general metabolic well-being and balanced living.

Inactive: Alcohol Base to Preserve Remedy

ACTIVE INGREDIENT

Acidum phosphoricum 7X: 0.20ml

Cephalandra indica Ø: 1.20ml

Gymnema sylvestre Ø: 1.20ml

Momordica charantia Ø: 0.40ml

Syzygium jambolanum Ø: 0.50ml

Keep all supplements away from Children.

PURPOSE

Traditionally used in homeopathy to support general metabolic well-being and balanced living.

Warnings:
Keep all supplements away from Children.
If you have any reaction to this product that
is not positive, discontinue use.

Entire package label